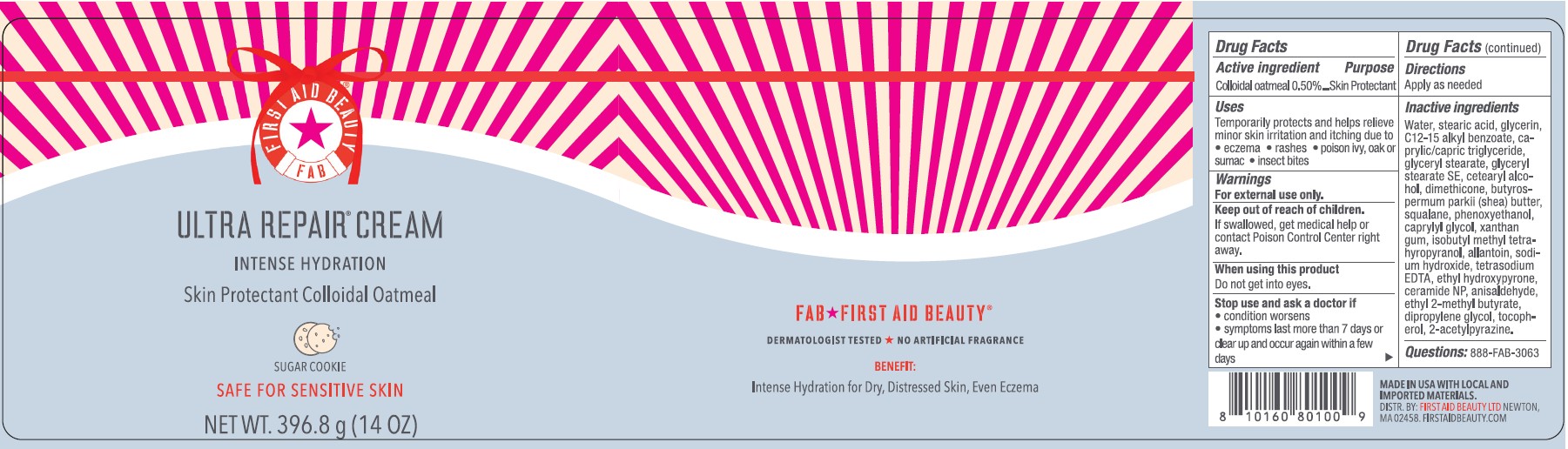 DRUG LABEL: First Aid Beauty FAB Ultra Repair Skin Protectant Cookie Dough
NDC: 84126-211 | Form: CREAM
Manufacturer: The Procter & Gamble Manufacturing Company
Category: otc | Type: HUMAN OTC DRUG LABEL
Date: 20251208

ACTIVE INGREDIENTS: OATMEAL 0.5 g/100 g
INACTIVE INGREDIENTS: CETEARYL ALCOHOL; TOCOPHEROL; GLYCERYL STEARATE SE; SQUALANE; DIMETHICONE; TETRASODIUM EDTA; C12-15 ALKYL BENZOATE; CAPRYLYL GLYCOL; PHENOXYETHANOL; BUTYROSPERMUM PARKII (SHEA) BUTTER; WATER; GLYCERIN; ALLANTOIN; GLYCERYL STEARATE; CAPRYLIC/CAPRIC TRIGLYCERIDE; STEARIC ACID; XANTHAN GUM; CERAMIDE NP; ISOBUTYL METHYL TETRAHYDROPYRANOL; SODIUM HYDROXIDE; ANISALDEHYDE; 2-ACETYLPYRAZINE; DIPROPYLENE GLYCOL; ETHYL 2-METHYLBUTYRATE; ETHYL HYDROXYPYRONE

First Aid Beauty FAB Ultra Repair Cream Skin Protectant Cookie Dough

Drug Facts

Active ingredients

Colloidal Oatmeal 0.5%

Purpose

Skin Protectant

Uses

- Temporarily protects and helps relieve minor skin irritation and itching due to eczema, rashes, poison ivy, oak or sumac, insect bites

Warnings

For external use only.

Keep out of reach of children. If swallowed, get medical help or contact a Poison Control Center right away.

WHEN USING

Do not get into eyes.

Stop use and ask a doctor if condition worsens, symptoms last more than 7 days or clear up and occur again within a few days

Directions

Apply as needed

INACTIVE INGREDIENT

Water, stearic acid, glycerin, C12-15 alkyl benzoate, caprylic/capric triglyceride, glyceryl stearate, glyceryl stearate SE, cetearyl alcohol, dimethicone, butyrospermum parkii (shea) butter, squalene, phenoxyethanol, caprylyl glycol. xanthan gum, isobutyl methyl tetrahyropyranol allantoin, sodium hydroxide, tetrasodium EDTA, ethyl hydroxypyrone, ceramide NP, anisaldehyde, ethyl 2-methylbutyrate, dipropylene glycol, tocopherol, 2-acetylpyrazine

Questions:

888-FAB-3063

MADE IN USA

FIRST AID BEAUTY LTD

NEWTON, MA 02458

WWW.FIRSTAIDBEAUTY.COM

PRINCIPAL DISPLAY PANEL - 14.0 oz (396.8 g)

First Aid Beauty

FAB

Ultra Repair® Cream

Intense Hydration

Skin Protectant Colloidal Oatmeal

Sugar Cookie

Net Wt. 14.0 oz (396.8 g)